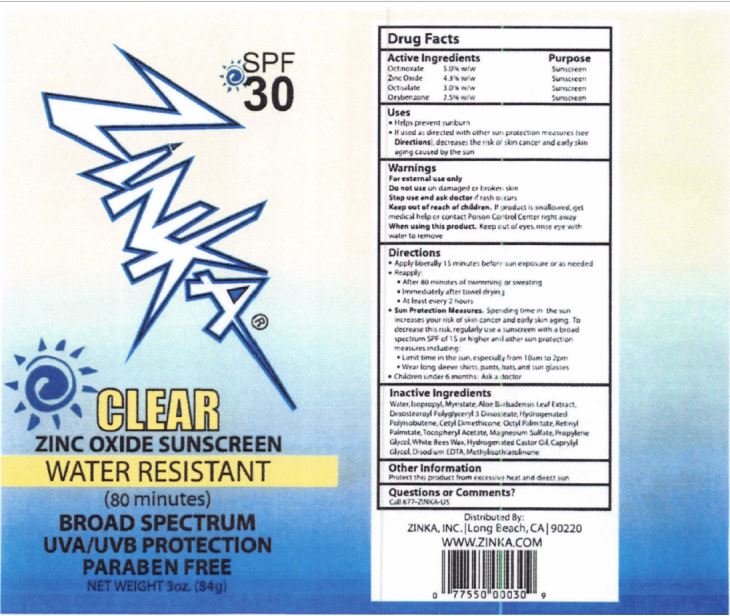 DRUG LABEL: Zinka Clear Zinc Oxide Sunscreen
NDC: 52993-001 | Form: LOTION
Manufacturer: Zinka, Inc.
Category: otc | Type: HUMAN OTC DRUG LABEL
Date: 20251111

ACTIVE INGREDIENTS: OCTINOXATE 50 mg/1 g; ZINC OXIDE 43 mg/1 g; OCTISALATE 30 mg/1 g; OXYBENZONE 25 mg/1 g
INACTIVE INGREDIENTS: WATER; ALOE VERA LEAF; ISOPROPYL MYRISTATE; HYDROGENATED POLYBUTENE (370 MW); DIISOSTEAROYL POLYGLYCERYL-3 DIMER DILINOLEATE; ETHYLHEXYL PALMITATE; CETYL DIMETHICONE 150; MAGNESIUM SULFATE ANHYDROUS; WHITE WAX; HYDROGENATED CASTOR OIL; EDETATE DISODIUM; .ALPHA.-TOCOPHEROL ACETATE; VITAMIN A PALMITATE; PROPYLENE GLYCOL; CAPRYLYL GLYCOL; METHYLISOTHIAZOLINONE

Zinka Clear Zinc Oxide Sunscreen

Active Ingredients

Octinoxate 5.0% w/w

Zinc Oxide 4.3% w/w

Octisalate 3.0% w/w

Oxybenzone 2.5% w/w

Purposes

Sunscreen

Uses

- Helps prevent sunburn and skin damage caused by UVA/UVB exposure
- Higher SPF gives more sunburn protection

Warnings

For external use only

Keep out of reach of children. If product is swallowed, get medical help or contact Poison Control Center right away.

When using this product

- Keep out of eyes. Rinse with water to remove
- Do not use if allergic to any ingredient
- Keep out of reach of children
- If swallowed, contact Poison Control Center immediately

Stop use and ask doctor if

- Rash or irritation develops and lasts

Directions

- Apply liberally 20 minutes before sun exposure to dry skin
- Reapply to dry skin after toweling, swimming or sweating
- For children under 6 months of age: Ask a doctor

Other information

Sun alert: Limiting sun exposure, wearing protective clothing, and using sunscreen may reduce the risk of skin aging, skin cancer, and other harmful effects of the sun.

Inactive Ingredients

Water, Isopropyl Myristate, Aloe Barbadensis Leaf Extract, Diisostearoyl Polyglyceryl-3 Diisostearate, Hydrogenated Polyisobutene, Cetyl Dimethicone, Octyl Palmitate, Retinyl Palmitate, Tocopheryl Acetate, Magnesium Sulfate, Propylene Glycol, White Bees Wax, Hydrogenated Castor Oil, Caprylyl Glycol, Disodium EDTA, Methylisothiazolinone